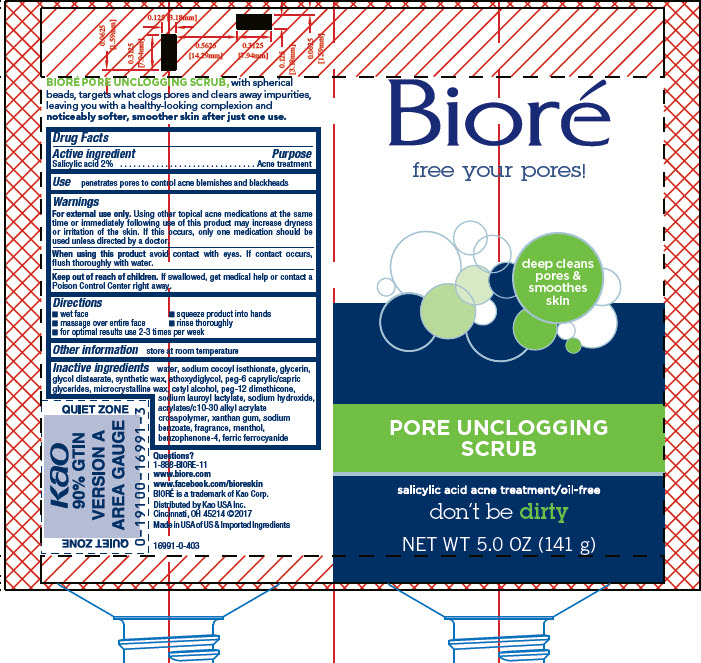 DRUG LABEL: Biore
NDC: 10596-161 | Form: LIQUID
Manufacturer: Kao USA Inc.
Category: otc | Type: HUMAN OTC DRUG LABEL
Date: 20250828

ACTIVE INGREDIENTS: SALICYLIC ACID 2.8 g/141 g
INACTIVE INGREDIENTS: PEG-6 CAPRYLIC/CAPRIC GLYCERIDES; CARBOMER INTERPOLYMER TYPE A (ALLYL SUCROSE CROSSLINKED); WATER; SODIUM COCOYL ISETHIONATE; GLYCERIN; GLYCOL DISTEARATE; SYNTHETIC WAX (1200 MW); DIETHYLENE GLYCOL MONOETHYL ETHER; MICROCRYSTALLINE WAX; CETYL ALCOHOL; PEG-12 DIMETHICONE (300 CST); SODIUM HYDROXIDE; SODIUM LAUROYL LACTYLATE; XANTHAN GUM; MENTHOL; SULISOBENZONE; FERRIC FERROCYANIDE; SODIUM BENZOATE

Biore Pore Unclogging Scrub

BIORE PORE UNCLOGGING SCRUB, with spherical beads, targets what clogs pores and clears away impurities, leaving you with a healthy-looking complexion and noticeably softer, smoother skin after just one use.

Drug Facts

Active ingredient

Salicylic Acid 2%

Purpose

Acne treatment

Use

penetrates pores to control acne blemishes and blackheads

WARNINGS

Warnings For external use only. Using other topical acne medication at the same time or immediately following use of this product may increase dryness or irritation of the skin. If this occurs, only one medication should be used unless directed by a doctor.

When using this product avoid contact with eyes. If contact occurs, flush thoroughly with water.

Keep out of reach of children. If swallowed, get medical help or contact a Poison Control Center right away.

Directions

- wet face
- squeeze product into hands
- massage over entire face
- rinse thoroughly
- for optimal results use 2-3 times per week

Other information

store at room temperature

INACTIVE INGREDIENT

Inactive ingredients water, sodium cocoyl isethionate, glycerin, glycol disearate, synthetic wax, ethoxydiglycol, PEG-6 caprylic/capric glycerides, microcrystalline wax, cetyl alcohol, PEG-12 dimethicone, sodium lauroyl lactylate, sodium hydroxide, acrylates/C10-30 alkyl acrylate crosspolymer, xanthan gum, sodium benzoate, fragrance, menthol, benzophenone-4, ferric ferrocyanide

Questions?

1-888-BIORE-11

www.biore.com

BIORE' is a trademark of Kao Corp.

Distributed by Kao USA Inc.
Cincinnati, OH 45214 ©2017
Made in USA of US & Imported Ingredients

PACKAGE LABEL

Biore

free your pores!

deep cleans pores & smoothes skin

PORE UNCLOGGING SCRUB

salicylic acid acne treatment/oil-free

don't be dirty

NET WT 5.0 OZ (141 g)